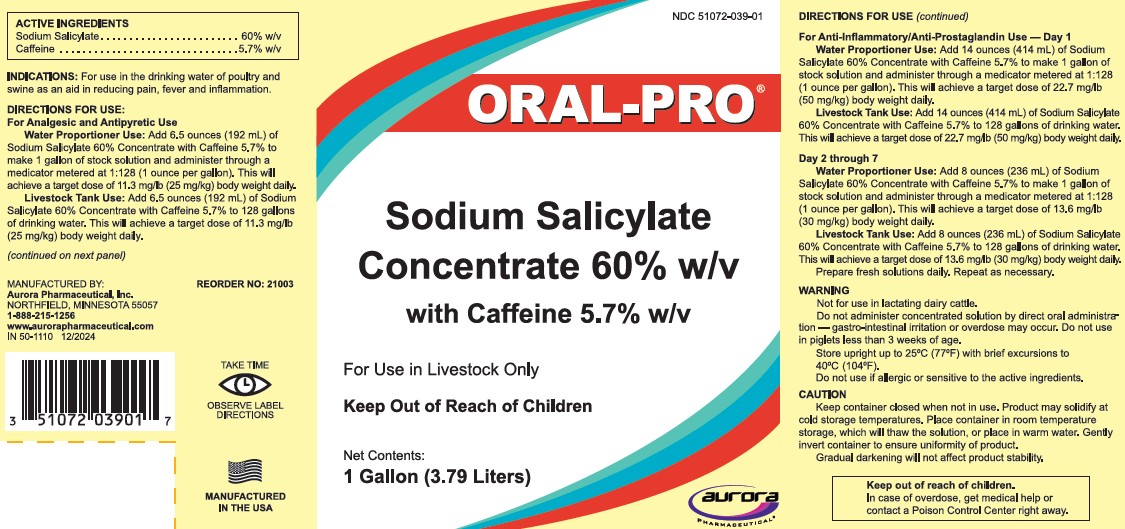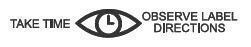 DRUG LABEL: ORAL-PRO SODIUM SALICYLATE
NDC: 51072-039 | Form: SOLUTION
Manufacturer: Aurora Pharmaceutical, Inc.
Category: animal | Type: OTC ANIMAL DRUG LABEL
Date: 20250529

ACTIVE INGREDIENTS: SODIUM SALICYLATE 60 g/100 mL; CAFFEINE 5.7 g/100 mL

ORAL-PRO®
Sodium Salicylate
Concentrate 60% w/v
with Caffeine 5.7% w/v

DESCRIPTION

ACTIVE INGREDIENTS
Sodium Salicylate | 60% w/v
Caffeine | 5.7% w/v

INDICATIONS

For use in the drinking water of poultry and swine as an aid in reducing pain, fever and inflammation.

DIRECTIONS FOR USE

For Analgesic and Antipyretic Use

Water Proportioner Use:

Add 6.5 ounces (192 mL) of Sodium Salicylate 60% Concentrate with Caffeine 5.7% to make 1 gallon of stock solution and administer through a medicator metered at 1:128 (1 ounce per gallon). This will achieve a target dose of 11.3 mg/lb (25 mg/kg) body weight daily.

Livestock Tank Use:

Add 6.5 ounces (192 mL) of Sodium Salicylate 60% Concentrate with Caffeine 5.7% to 128 gallons of drinking water. This will achieve a target dose of 11.3 mg/lb (25 mg/kg) body weight daily.

For Anti-Inflammatory/Anti-Prostaglandin Use — Day 1

Water Proportioner Use:

Add 14 ounces (414 mL) of Sodium Salicylate 60% Concentrate with Caffeine 5.7% to make 1 gallon of stock solution and administer through a medicator metered at 1:128 (1 ounce per gallon). This will achieve a target dose of 22.7 mg/lb (50 mg/kg) body weight daily.

Livestock Tank Use:

Add 14 ounces (414 mL) of Sodium Salicylate 60% Concentrate with Caffeine 5.7% to 128 gallons of drinking water. This will achieve a target dose of 22.7 mg/lb (50 mg/kg) body weight daily.

Day 2 through 7

Water Proportioner Use:

Add 8 ounces (236 mL) of Sodium Salicylate 60% Concentrate with Caffeine 5.7% to make 1 gallon of stock solution and administer through a medicator metered at 1:128 (1 ounce per gallon). This will achieve a target dose of 13.6 mg/lb (30 mg/kg) body weight daily.

Livestock Tank Use:

Add 8 ounces (236 mL) of Sodium Salicylate 60% Concentrate with Caffeine 5.7% to 128 gallons of drinking water. This will achieve a target dose of 13.6 mg/lb (30 mg/kg) body weight daily.

Prepare fresh solutions daily. Repeat as necessary.

Warning

Do not administer concentrated solution by direct oral administration — gastro-intestinal irritation or overdose may occur. Do not use in piglets less than 3 weeks of age.

STORAGE AND HANDLING

Store upright up to 25° C (77° F) with brief excursions to 40° C (104° F).

Do not use if allergic or sensitive to the active ingredients.

Caution

Keep container closed when not in use. Product may solidify at cold storage temperatures. Place container in room temperature storage, which will thaw the solution, or place in warm water. Gently invert container to ensure uniformity of product.

Gradual darkening will not affect product stability.

Keep out of reach of children.

In case of overdose, get medical help or contact a Poison Control Center right away.

MANUFACTURED IN THE USA

REORDER NO: 21003

MANUFACTURED BY:
Aurora Pharmaceutical, Inc.
NORTHFIELD, MINNESOTA 55057
1-888-215-1256
www.aurorapharmaceutical.com
IN 50-1110 12/2024

PRINCIPAL DISPLAY PANEL - 3.79 Liter Bottle Label

NDC 51072-039-01

ORAL-PRO®

Sodium Salicylate
Concentrate 60% w/v
with Caffeine 5.7% w/v

For Use in Livestock Only

Keep Out of Reach of Children

Net Contents:
1 Gallon (3.79 Liters)

AURORA PHARMACEUTICAL®